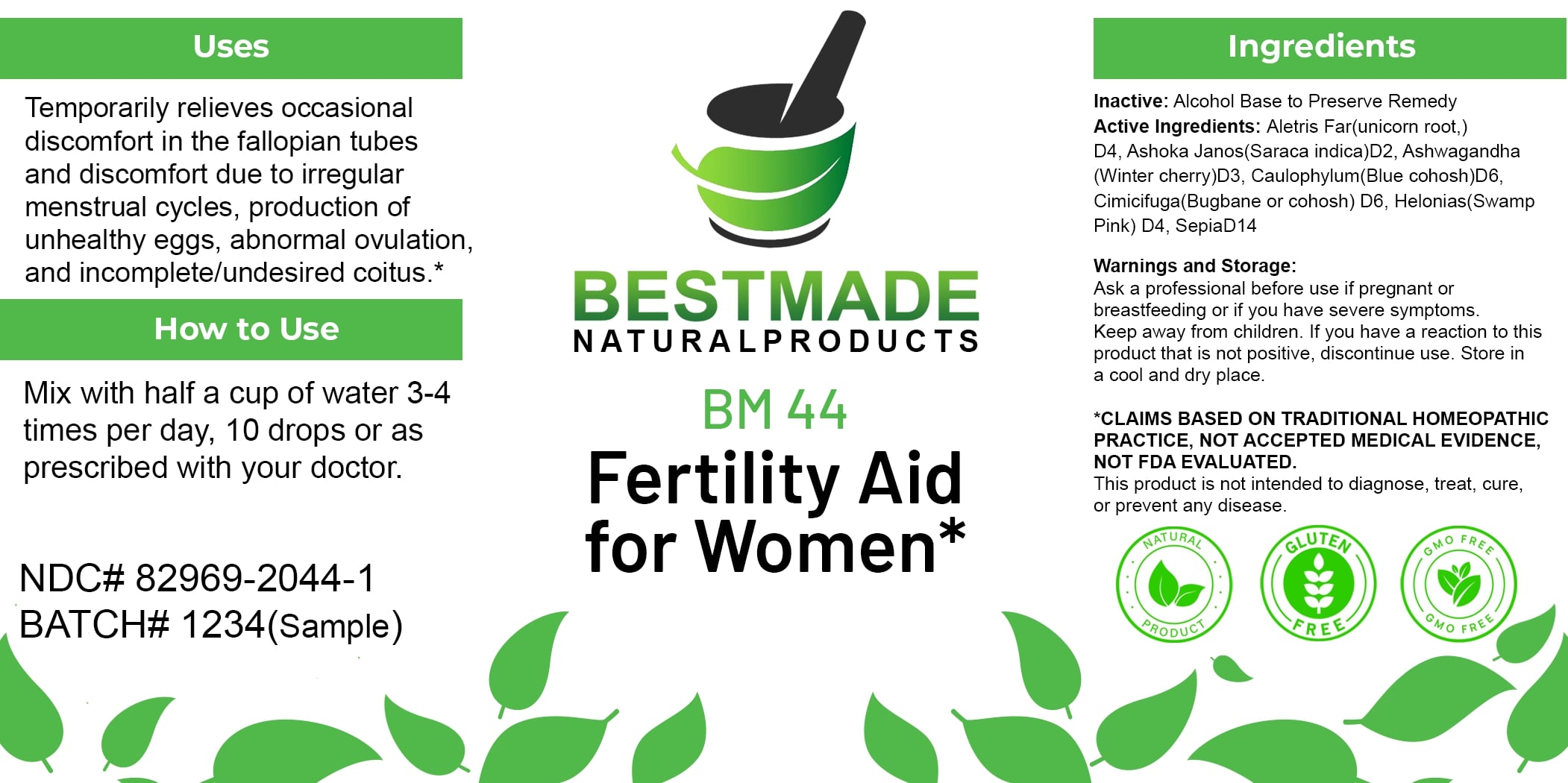 DRUG LABEL: Bestmade Natural Products BM44
NDC: 82969-2044 | Form: LIQUID
Manufacturer: Bestmade Natural Products
Category: homeopathic | Type: HUMAN OTC DRUG LABEL
Date: 20250123

ACTIVE INGREDIENTS: ALETRIS FARINOSA ROOT 30 [hp_C]/30 [hp_C]; WITHANIA SOMNIFERA WHOLE 30 [hp_C]/30 [hp_C]; CAULOPHYLLUM THALICTROIDES ROOT 30 [hp_C]/30 [hp_C]; BLACK COHOSH 30 [hp_C]/30 [hp_C]; CHAMAELIRIUM LUTEUM ROOT 30 [hp_C]/30 [hp_C]; SEPIA OFFICINALIS WHOLE 30 [hp_C]/30 [hp_C]
INACTIVE INGREDIENTS: ALCOHOL 30 [hp_C]/30 [hp_C]

BM44

DOSAGE AND ADMINISTRATION

How to Use

Mix with half a cup of water 3-4 times per day. 10 drops or as prescribed with your doctor.

INACTIVE INGREDIENT

Ingredients

Inactive: Alcohol Base to Preserve Remedy

ACTIVE INGREDIENT

Active Ingredients: Aletris Far (unicorn root,) D4, Ashoka Janos (Saraca indica) D2, Ashwagandha (Winter cherry) D3, Caulophylum (Blue cohosh) D6, Cimicifuga (Bugbane or cohosh) D6, Helonias (Swamp Pink) D4, Sepia D14

Uses

Temporarily relieves occasional discomfort in the fallopian tubes and discomfort due to irregular menstrual cycles, production of unhealthy eggs, abnormal ovulation, and incomplete/undesired coitus.*

*CLAIMS BASED ON TRADITIONAL HOMEOPATHIC PRACTICE, NOT ACCEPTED MEDICAL EVIDENCE, NOT FDA EVALUATED.

This product is not intended to diagnose, treat, cure, or prevent any disease.

Uses

Temporarily relieves occasional discomfort in the fallopian tubes and discomfort due to irregular menstrual cycles, production of unhealthy eggs, abnormal ovulation, and incomplete/undesired coitus.*

*CLAIMS BASED ON TRADITIONAL HOMEOPATHIC PRACTICE, NOT ACCEPTED MEDICAL EVIDENCE, NOT FDA EVALUATED.

This product is not intended to diagnose, treat, cure, or prevent any disease.

KEEP OUT OF REACH OF CHILDREN

Warnings and Storage:

Ask a professional before use if pregnant or breastfeeding or if you have severe symptoms. Keep away from children. If you have a reaction to this product that is not positive, discontinue use. Store in a cool and dry place.

Warnings and Storage:

Ask a professional before use if pregnant or breastfeeding or if you have severe symptoms. Keep away from children. If you have a reaction to this product that is not positive, discontinue use. Store in a cool and dry place.

*CLAIMS BASED ON TRADITIONAL HOMEOPATHIC PRACTICE, NOT ACCEPTED MEDICAL EVIDENCE, NOT FDA EVALUATED.

This product is not intended to diagnose, treat, cure, or prevent any disease.

Entire package label